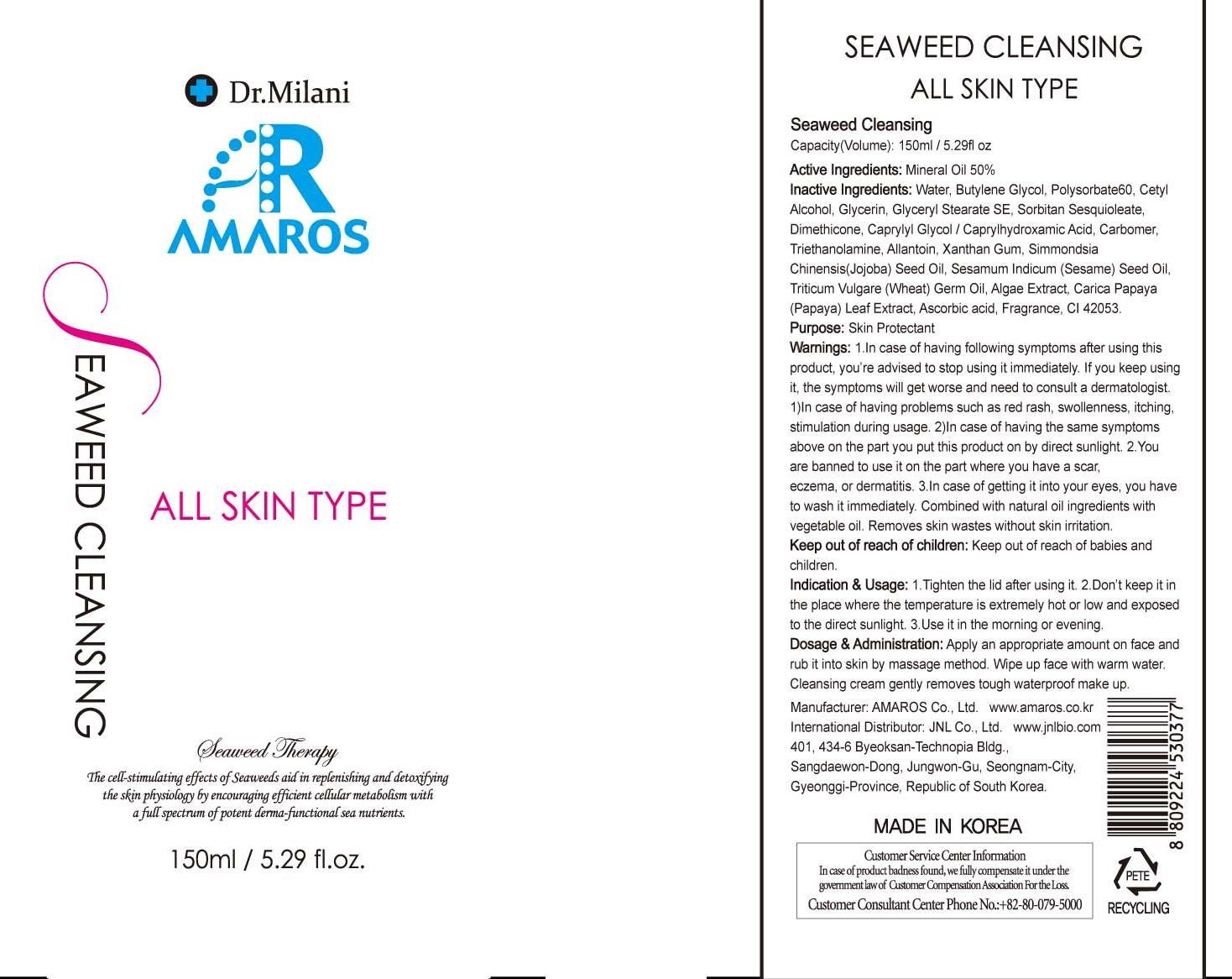 DRUG LABEL: Seaweed Cleansing
NDC: 60899-050 | Form: LIQUID
Manufacturer: AMAROS CO., LTD.
Category: otc | Type: HUMAN OTC DRUG LABEL
Date: 20190411

ACTIVE INGREDIENTS: Mineral Oil 75 mg/150 mL
INACTIVE INGREDIENTS: Water; Butylene Glycol

ACTIVE INGREDIENT

Active Ingredient: Mineral Oil 50%

INACTIVE INGREDIENT

Inactive Ingredients: Water, Butylene Glycol, Polysorbate60, Cetyl Alcohol, Glycerin, Glyceryl Stearate SE, Sorbitan Sesquioleate, Dimethicone, Caprylyl Glycol / Caprylhydroxamic Acid, Carbomer, Triethanolamine, Allantoin, Xanthan Gum, Simmondsia Chinensis(Jojoba) Seed Oil, Sesamum Indicum (Sesame) Seed Oil, Triticum Vulgare (Wheat) Germ Oil, Algae Extract, Carica Papaya (Papaya) Leaf Extract, Ascorbic acid, Fragrance, CI 42053.

PURPOSE

Purpose: Skin protectant

WARNINGS

Warnings: 1. In case of having following symptoms after using this product, you're advised to stop using it immediately. If you keep using it, the symptoms will get worse and need to consult a dermatologist . 1) In case of having problems such as red rash, swollenness, itching, stimulation during usage. 2) In case of having the same symptoms above on the part you put this product on by direct sunlight. 2. You are banned to use it on the part where you have a scar, eczema, or dermatitis. 3. In case of getting it into your eyes, you have to wash it immediately.

Keep out of reach of children: Keep out of reach of babies and children.

INDICATIONS AND USAGE

Indication and Usage: 1. Tighten the lid after using it. 2. Don't keep it in the place where the temperature is extremely hot or low and exposed to the direct sunlight.3. Use it in the morning or evening.

Dosage and Administration: Apply an appropriate amount on face and rub it into skin by massage method. Wipe up face with warm water. Cleansing cream gently removes tough waterproof make up.